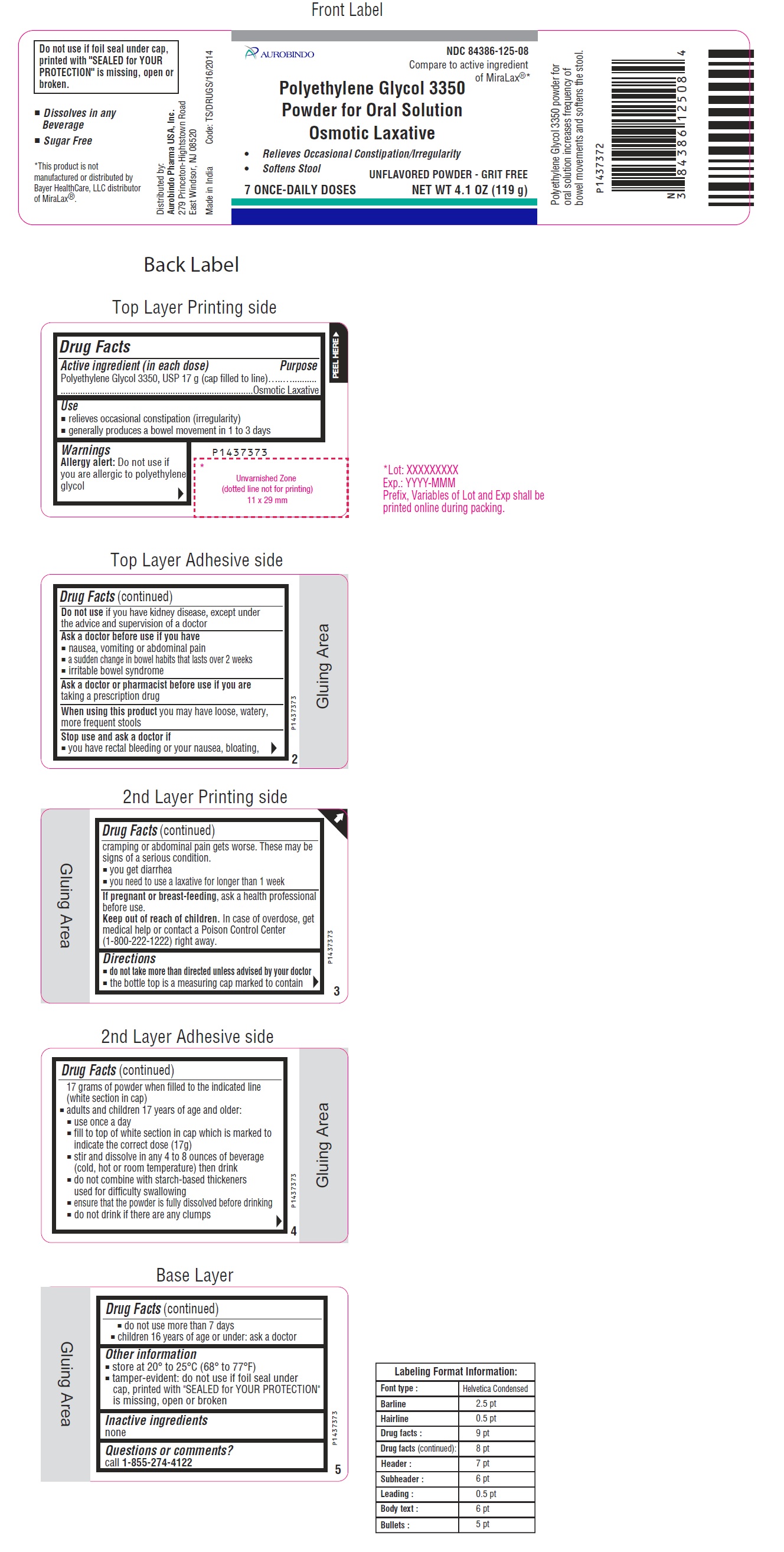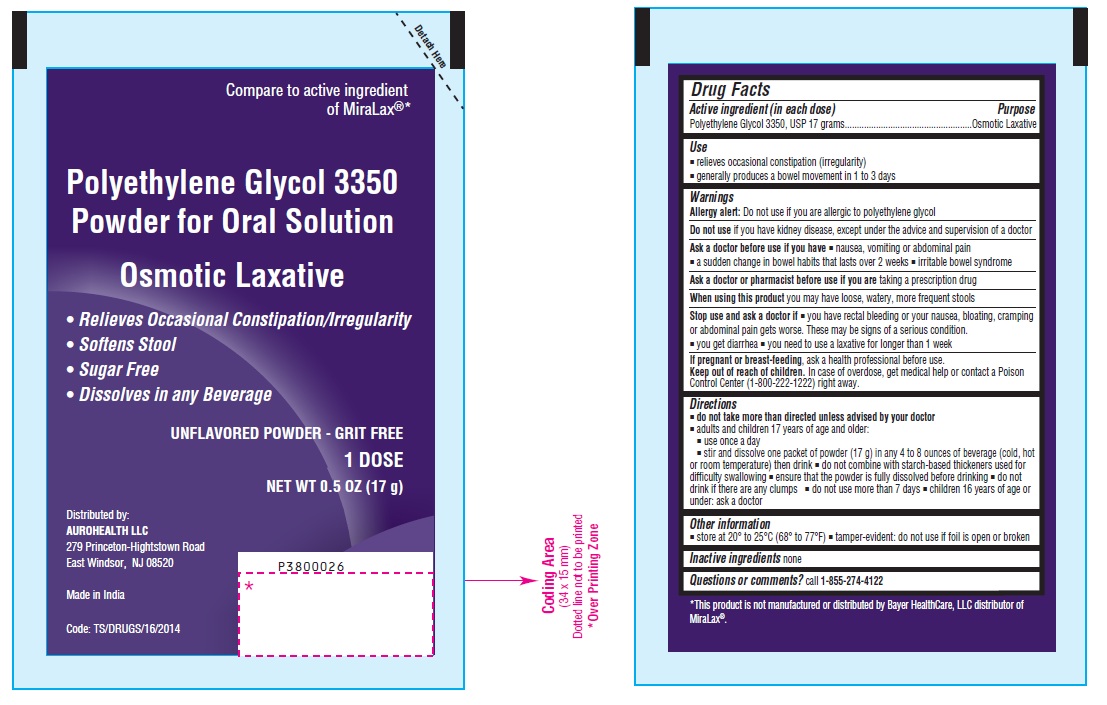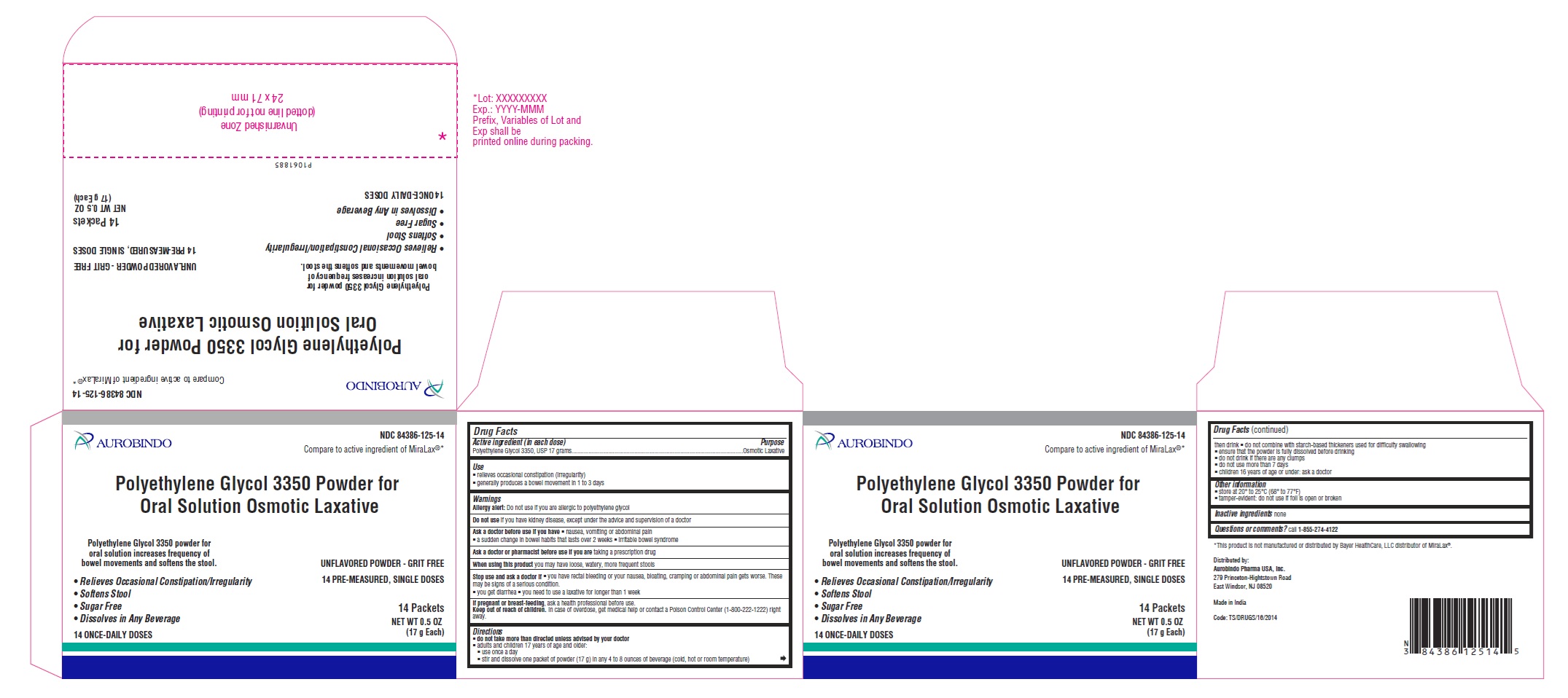 DRUG LABEL: Polyethylene Glycol 3350
NDC: 84386-125 | Form: POWDER, FOR SOLUTION
Manufacturer: Aurobindo Pharma Limited
Category: otc | Type: Human OTC Drug Label
Date: 20260107

ACTIVE INGREDIENTS: POLYETHYLENE GLYCOL 3350 17 g/17 g

Polyethylene Glycol 3350 Powder for Oral Solution

Drug Facts

Active ingredient (in each dose)
Polyethylene Glycol 3350, USP 17 g (cap filled to line)

Purpose

Osmotic Laxative

Use

- relieves occasional constipation (irregularity)
- generally produces a bowel movement in 1 to 3 days

Warnings

Allergy alert: Do not use if you are allergic to polyethylene glycol

Do not use if you have kidney disease, except under the advice and supervision of a doctor

Ask a doctor before use if you have

- nausea, vomiting or abdominal pain
- a sudden change in bowel habits that lasts over 2 weeks
- irritable bowel syndrome

Ask a doctor or pharmacist before use if you are taking a prescription drug

When using this product you may have loose, watery, more frequent stools

Stop use and ask a doctor if

- you have rectal bleeding or your nausea, bloating, cramping or abdominal pain gets worse. These may be signs of a serious condition.
- you get diarrhea
- you need to use a laxative for longer than 1 week

PREGNANCY OR BREAST FEEDING

If pregnant or breast-feeding, ask a health professional before use.

Keep out of reach of children.

In case of overdose, get medical help or contact a Poison Control Center (1-800-222-1222) right away.

Directions

- do not take more than directed unless advised by your doctor
- the bottle top is a measuring cap marked to contain 17 grams of powder when filled to the indicated line (white section in cap)
- adults and children 17 years of age and older:
  - use once a day
  - fill to top of white section in cap which is marked to indicate the correct dose (17g)
  - stir and dissolve in any 4 to 8 ounces of beverage (cold, hot or room temperature) then drink
  - do not combine with starch-based thickeners used for difficulty swallowing
  - ensure that the powder is fully dissolved before drinking
  - do not drink if there are any clumps
  - do not use more than 7 days
- children 16 years of age or under: ask a doctor

Other information

- store at 20° to 25°C (68° to 77°F)
- tamper-evident: do not use if foil seal under cap, printed with "SEALED for YOUR PROTECTION" is missing, open or broken

Inactive ingredients

none
Questions or comments?
call 1-855-274-4122
Distributed by:
Aurobindo Pharma USA, Inc.
279 Princeton-Hightstown Road
East Windsor, NJ 08520
Made in India

Code: TS/DRUGS/16/2014

PACKAGE LABEL-PRINCIPAL DISPLAY PANEL - 119 g Bottle Label

AUROBINDO
NDC 84386-125-08
Compare to active ingredient
of MiraLax®*
Polyethylene Glycol 3350
Powder for Oral Solution
Osmotic Laxative

- Relieves Occasional Constipation/Irregularity
- Softens Stool

UNFLAVORED POWDER - GRIT FREE
7 ONCE-DAILY DOSES NET WT 4.1 OZ (119 g)

PACKAGE LABEL-PRINCIPAL DISPLAY PANEL - 17 g Sachet Label

Compare to active ingredient
of MiraLax®*
Polyethylene Glycol 3350
Powder for Oral Solution
Osmotic Laxative

- Relieves Occasional Constipation/Irregularity
- Softens Stool
- Sugar Free
- Dissolves in any Beverage

UNFLAVORED POWDER - GRIT FREE
1 DOSE
NET WT 0.5 oz (17 g)

PACKAGE LABEL-PRINCIPAL DISPLAY PANEL - 17 g Sachet Carton Label

AUROBINDO
NDC 84386-125-14
Compare to active ingredient
of MiraLax®*
Polyethylene Glycol 3350
Powder for Oral Solution
Osmotic Laxative
Polyethylene Glycol 3350 powder for
oral solution increases frequency of
bowel movements and softness the stool.

- Relieves Occasional Constipation/Irregularity
- Softens Stool
- Sugar Free
- Dissolves in Any Beverage

14 ONCE-DAILY DOSES

UNFLAVORED POWDER - GRIT FREE
14 PRE-MEASURED, SINGLE DOSES
14 Packets
NET WT 0.5 oz
(17 g Each)